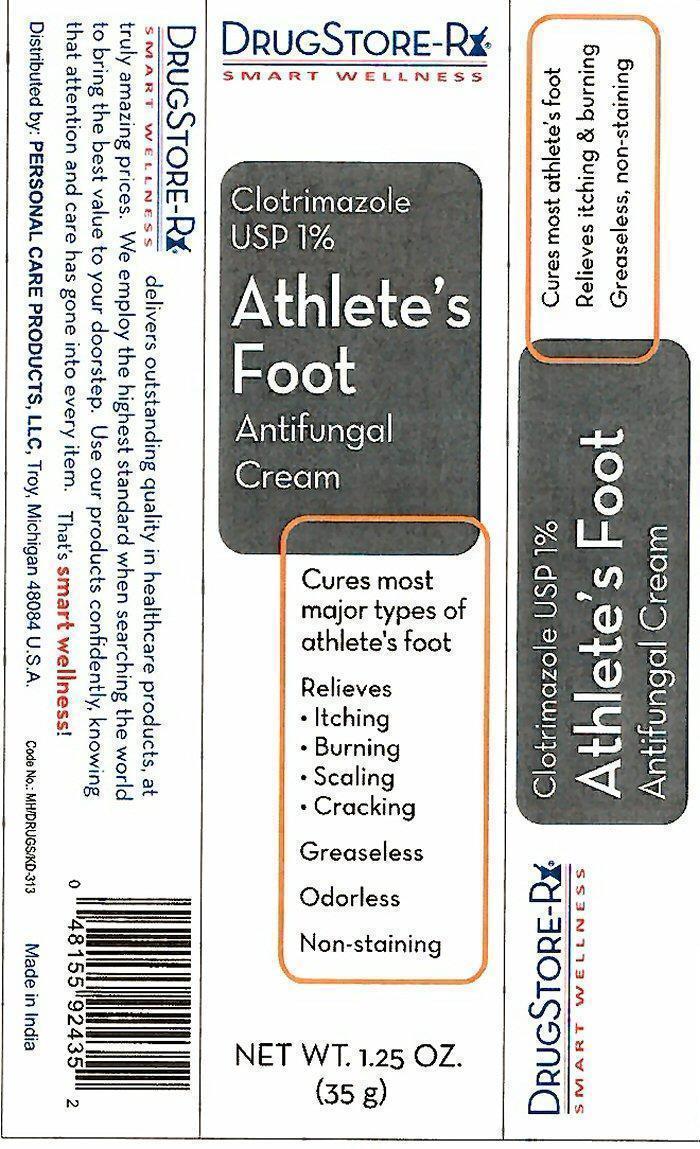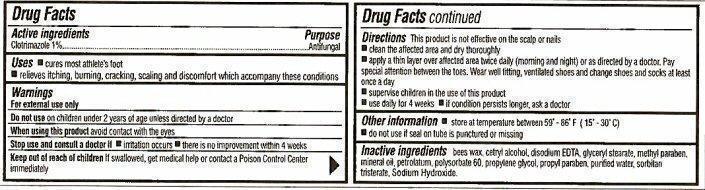 DRUG LABEL: Athletes Foot Antifungal
NDC: 29500-2435 | Form: CREAM
Manufacturer: Personal Care Products, Inc.
Category: otc | Type: HUMAN OTC DRUG LABEL
Date: 20200725

ACTIVE INGREDIENTS: CLOTRIMAZOLE 350 mg/35 g
INACTIVE INGREDIENTS: YELLOW WAX; CETYL ALCOHOL; EDETATE DISODIUM; GLYCERYL MONOSTEARATE; METHYLPARABEN; MINERAL OIL; PETROLATUM; POLYSORBATE 60; PROPYLENE GLYCOL; PROPYLPARABEN; WATER; SORBITAN TRISTEARATE; SODIUM HYDROXIDE

Active ingredients

Drug Facts
Clotrimazole 1%

Purpose

Antifungal

Keep out of reach of children. If swallowed, get medical help or contact a Poison Control Center immediately.

Uses

- cures most athlete's foot
- relieves itching, burning, cracking, scaling and discomfort which accompany these conditions

Warnings

For external use only
Do not use on children under 2 years of age unless directed by a doctor
When using this product avoid contact with the eyes
Stop use and consult a doctor if

- irritation occurs
- there is no improvement within 2 weeks

Directions

This product is not effective on the scalp or nails

- clean the affected area and dry thoroughly
- apply a thin layer over affected area twice daily (morning and night) or as directed by a doctor. Pay special attention between the toes. Wear well fitting, ventilated shoes and change shoes and socks at least once a day.
- supervise children in the use of this product
- use daily for 4 weeks
- if condition persists longer, ask a doctor

Other information

- store at temperature between 59° - 86° F (15° - 30° C)
- do not use if seal on tube is punctured or missing

Inactive ingredients

bees wax, cetryl alcohol, disodium EDTA, glyceryl stearate, methyl paraben, mineral oil, petrolatum, polysorbate 60, propylene glycol, propyl paraben, purified water, sorbitan tristerate, Sodium Hydroxide.

Product Label

DRUGSTORE-Rx
SMART WELLNESS
Clotrimazole USP 1%
Athlete's Foot
Antifungal Cream
Cures most major types of athlete's foot
Relieves

- Itching
- Burning
- Scaling
- Cracking

Greaseless

Odorless
Non-staining
NET WT. 1.25 OZ. (35 g)
DRUGSTORE-Rx
SMART WELLNESS delivers outstanding quality in healthcare products, at truly amazing prices. We employ the highest standard when searching the world to bring the best value to your doorstep. Use our products confidently, knowing that attention and care has gone into every item. That's smart wellness!
Distributed by: PERSONAL CARE PRODUCTS, LLC
Troy, Michigan 48084 U.S.A.
Code No. MH/DRUGS/KD-313 Made in India